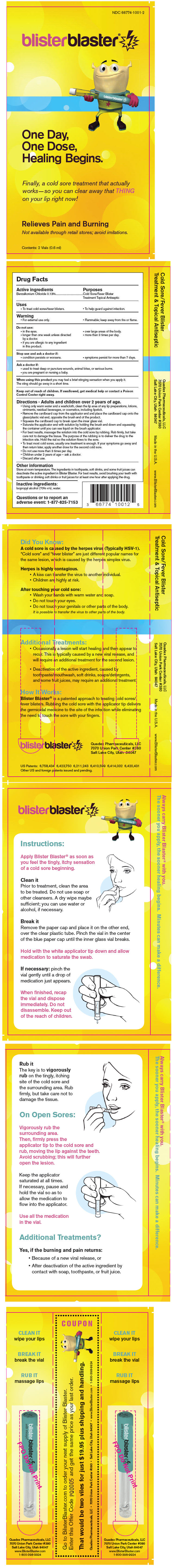 DRUG LABEL: Blister Blaster
NDC: 66774-1001 | Form: LIQUID
Manufacturer: Quadex Pharmaceuticals, LLC
Category: otc | Type: HUMAN OTC DRUG LABEL
Date: 20110708

ACTIVE INGREDIENTS: Benzalkonium chloride 0.12 g/100 mL
INACTIVE INGREDIENTS: Isopropyl Alcohol 70 mL/100 mL; Water

blisterblaster®

Drug Facts

Active ingredients

Benzalkonium Chloride 0.13%

Purposes

Cold Sore/Fever Blister Treatment Topical Antiseptic

Uses

- To treat cold sores/fever blisters.
- To help guard against infection.

Warning

- For external use only.
- Flammable; keep away from fire or flame.

Do not use:

- in the eyes.
- over large areas of the body.
- longer than one week unless directed by a doctor.
- more than 3 times per day.
- if you are allergic to any ingredient in this product.

Stop use and ask a doctor if:

- condition persists or worsens.
- symptoms persist for more than 7 days.

Ask a doctor if:

- used to treat deep or puncture wounds, animal bites, or serious burns.
- you are pregnant or nursing a baby.

When using this product you may feel a brief stinging sensation when you apply it. The sting should go away in a short time.

Keep out of reach of children. If swallowed, get medical help or contact a Poison Control Center right away.

Directions - Adults and children over 2 years of age

- Using only warm water and a washcloth, clean the lip area of any lip preparations, lotions, ointments, residual beverages, or cosmetics, including lipstick.
- Remove the cardboard cap from the applicator end and place the cardboard cap onto the glass/plastic vial end, opposite the brush end of the product.
- Squeeze the cardboard cap to break open the inner glass vial.
- Saturate the applicator end with solution by holding the brush end down and squeezing the container until you can see liquid on the brush applicator.
- For best results, massage the solution into the cold sore by rubbing. Rub firmly, but take care not to damage the tissue. The purpose of the rubbing is to deliver the drug to the infection site. Hold the vial so the solution flows to the sore.
- To treat most cold sores, usually one treatment is enough. If your symptoms go away and then return later, apply another dose for the second cold sore.
- Do not use more than 3 times per day.
- Children under 2 years of age — ask a doctor.
- Discard after use.

Other information

Store at room temperature. The ingredients in toothpaste, soft drinks, and some fruit juices can deactivate the active ingredient in Blister Blaster. For best results, avoid brushing your teeth with toothpaste or drinking soft drinks or fruit juices for at least one hour after applying the drug.

Inactive ingredients

Isopropyl alcohol (70% v/v), water.

QUESTIONS

Questions or to report an adverse event: 1-877-825-7153

PRINCIPAL DISPLAY PANEL - 0.6 ml Vial Blister Pack

NDC 66774-1001-2

blisterblaster®

One Day,
One Dose,
Healing Begins.

Finally, a cold sore treatment that actually
works—so you can clear away that THING
on your lip right now!

Relieves Pain and Burning

Not available through retail stores; avoid imitations.

Contents: 2 Vials (0.6 ml)